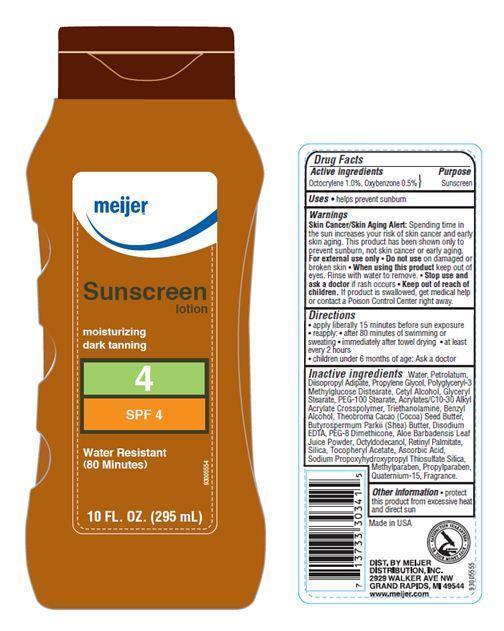 DRUG LABEL: Meijer Tropical SPF 4
NDC: 41250-013 | Form: LOTION
Manufacturer: Meijer Distribution Inc
Category: otc | Type: HUMAN OTC DRUG LABEL
Date: 20120101

ACTIVE INGREDIENTS: OCTOCRYLENE 1 mL/100 mL; OXYBENZONE 0.5 mL/100 mL
INACTIVE INGREDIENTS: WATER; PETROLATUM; DIISOPROPYL ADIPATE; PROPYLENE GLYCOL; CETYL ALCOHOL; GLYCERYL MONOSTEARATE; PEG-100 STEARATE; CARBOMER INTERPOLYMER TYPE A (55000 CPS); TROLAMINE; BENZYL ALCOHOL; COCOA BUTTER; SHEA BUTTER; EDETATE DISODIUM; PEG-8 DIMETHICONE; ALOE VERA LEAF; OCTYLDODECANOL; VITAMIN A PALMITATE; SILICON DIOXIDE; .ALPHA.-TOCOPHEROL ACETATE; ASCORBIC ACID; METHYLPARABEN; PROPYLPARABEN; QUATERNIUM-15

Drug Facts

Active Ingredients

Octocrylene 1.0
Oxybenzone 0.5

Purpose

Sunscreen

Uses

helps prevent sunburn

Warnings

Skin Cancer/Skin Aging Alert: Spending time in the sun increases your risk of skin cancer and early skin aging. This product has been shown only to prevent sunburn, not skin cancer or early aging.

For external use only. Do not use on damaged or broken skin.

When using this product

Keep out of eyes. Rinse with water to remove.

Stop use and ask a doctor

if rash occurs

Keep out of reach of children

If swallowed, get medical help or contact a Poison Control Center right away.

Directions

- apply liberally 15 minutes before sun exposure
- reapply
- after 80 minutes of swimming or sweating
- immediately after towel drying
- at least every 2 hours
- children under 6 months of age: Ask a doctor

Inactive Ingredients

Water, Petrolatum, Diisopropyl Adipate, Propylene Glycol, Polyglyceryl-3 Methylglucose Distearate, Cetyl Alcohol, Glyceryl Stearate, PEG-100 Stearate, Acrylates/C10-30 Alkyl Acrylate Crosspolymer, Triethanolamine, Benzyl Alcohol, Theobroma Cacao (Cocoa) Seed Butter, Butyrospermum Parkii (Shea) Butter, Disodium EDTA, PEG-8 Dimethicone, Aloe Barbadensis Leaf Juice Powder, Octyldodecanol, Retinyl Palmitate, Silica, Tocopheryl Acetate, Ascorbic Acid, Sodium Propoxyhydroxypropyl Thiosulfate Silica, Methylparaben, Propylparaben, Quaternium-15, Fragrance.

Other Information

protect this product from excessive heat and direct sun